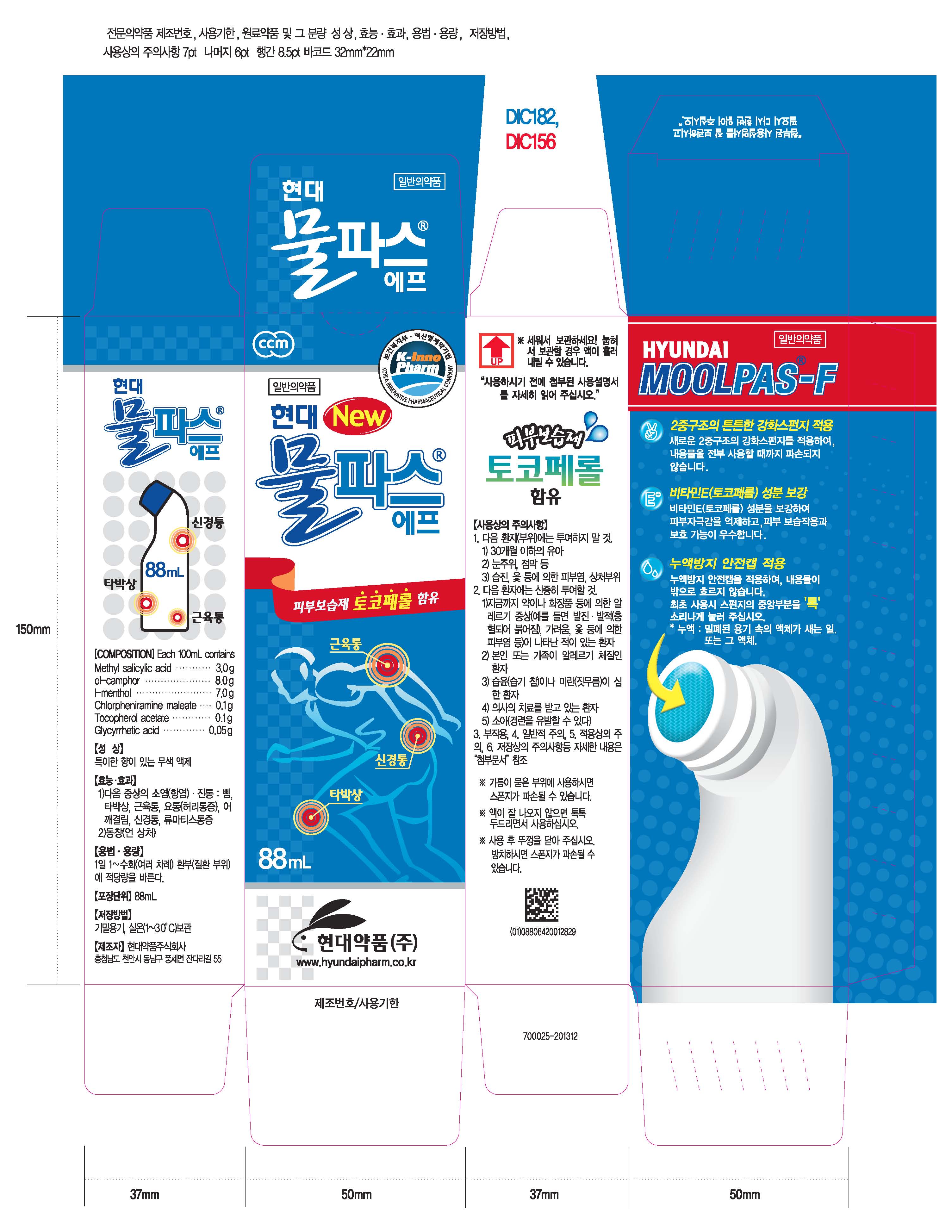 DRUG LABEL: Hyundai Moolpas F
NDC: 68994-3001 | Form: SOLUTION
Manufacturer: Scott Holdings Co., Ltd.
Category: otc | Type: HUMAN OTC DRUG LABEL
Date: 20140525

ACTIVE INGREDIENTS: METHYL SALICYLATE 3 g/100 mL
INACTIVE INGREDIENTS: MENTHOL; CAMPHOR (SYNTHETIC); CHLORPHENIRAMINE MALEATE; .ALPHA.-TOCOPHEROL ACETATE

Drug Facts

ACTIVE INGREDIENT

methyl salicylate

INACTIVE INGREDIENT

camphor, menthol, chlorpherol acetate, glycyrrhetic acid

PURPOSE

- antiinflammatory analgesic of the following symptoms: sprain, contusion, myosalgia, backache, shoulder discomfort, neuralgia, rheumarthritis- pernio

keep out or reach of the children

INDICATIONS AND USAGE

apply to the affected area once to several times a day

WARNINGS

avoid contact with eyes, if this product splashes in to your eyes, wash immediately with water

DOSAGE AND ADMINISTRATION

for external use only